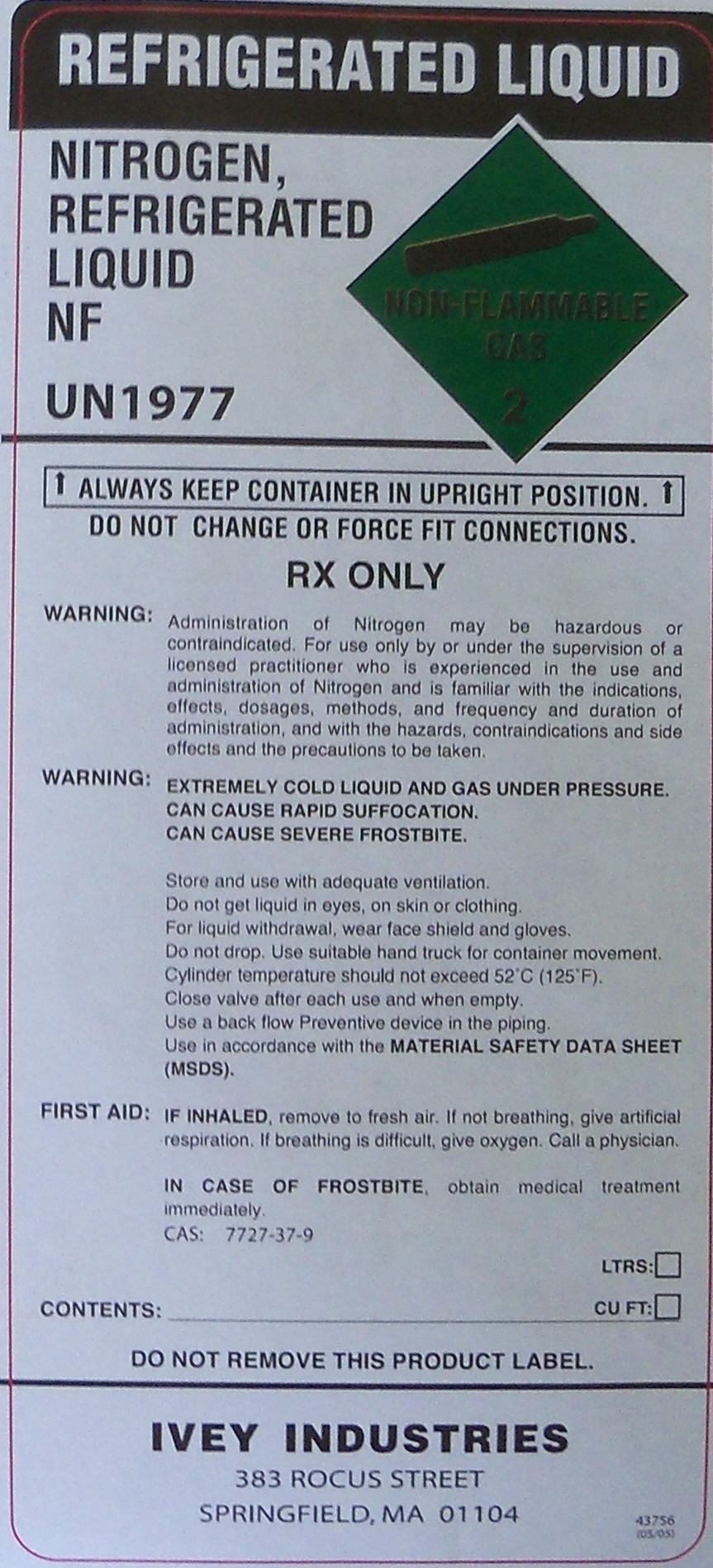 DRUG LABEL: nitrogen
NDC: 55065-004 | Form: LIQUID
Manufacturer: Ivey Industries
Category: prescription | Type: HUMAN PRESCRIPTION DRUG LABEL
Date: 20100503

ACTIVE INGREDIENTS: nitrogen 99 L/100 L

NITROGEN REFRIGERATED LIQUID NF UN1977

PACKAGE LABEL

NITROGEN REFRIGERATED LIQUID NF

UN 1077